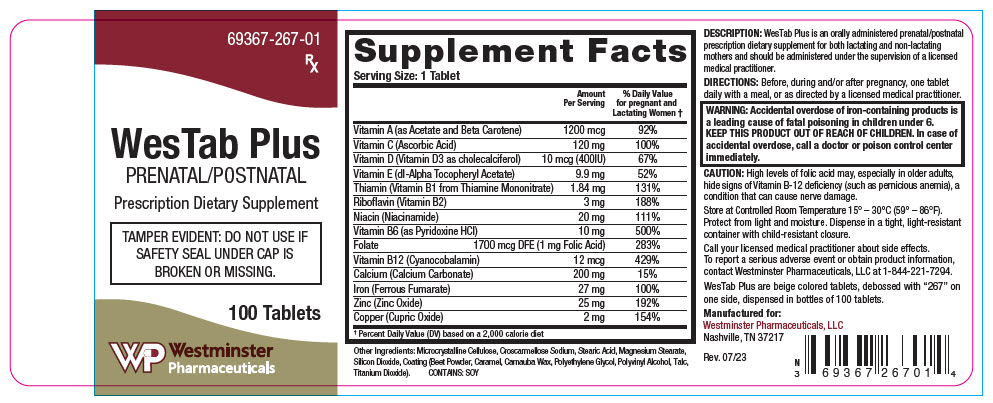 DRUG LABEL: WesTab Plus
NDC: 69367-267 | Form: TABLET
Manufacturer: Westminster Pharmaceuticals, LLC
Category: other | Type: DIETARY SUPPLEMENT
Date: 20231205

ACTIVE INGREDIENTS: VITAMIN A ACETATE 2000 [iU]/1 1; BETA CAROTENE 2000 [iU]/1 1; ASCORBIC ACID 120 mg/1 1; CHOLECALCIFEROL 400 [iU]/1 1; .ALPHA.-TOCOPHEROL ACETATE, DL- 9.9 mg/1 1; THIAMINE MONONITRATE 1.84 mg/1 1; RIBOFLAVIN 3 mg/1 1; NIACINAMIDE 20 mg/1 1; PYRIDOXINE HYDROCHLORIDE 10 mg/1 1; FOLIC ACID 1 mg/1 1; CYANOCOBALAMIN 12 ug/1 1; CALCIUM CARBONATE 200 mg/1 1; FERROUS FUMARATE 27 mg/1 1; ZINC OXIDE 25 mg/1 1; CUPRIC OXIDE 2 mg/1 1
INACTIVE INGREDIENTS: MICROCRYSTALLINE CELLULOSE; STEARIC ACID; CROSCARMELLOSE SODIUM; SILICON DIOXIDE; MAGNESIUM STEARATE; BEET; CARAMEL; CARNAUBA WAX; POLYETHYLENE GLYCOL, UNSPECIFIED; TITANIUM DIOXIDE; POLYVINYL ALCOHOL, UNSPECIFIED; TALC

WesTab Plus

STATEMENT OF IDENTITY

Supplement Facts
Serving Size: 1 Tablet
 | Amount Per Serving | % Daily Value for pregnant and Lactating Women [Percent Daily Value (DV) based on a 2,000 calorie diet]
Vitamin A (as Acetate and Beta Carotene) | 1200 mcg | 92%
Vitamin C (Ascorbic Acid) | 120 mg | 100%
Vitamin D (Vitamin D3 as cholecalciferol) | 10 mcg (400IU) | 67%
Vitamin E (dl-Alpha Tocopheryl Acetate) | 9.9 mg | 52%
Thiamin (Vitamin B1 from Thiamine Mononitrate) | 1.84 mg | 131%
Riboflavin (Vitamin B2) | 3 mg | 188%
Niacin (Niacinamide) | 20 mg | 111%
Vitamin B6 (as Pyridoxine HCl) | 10 mg | 500%
Folate | 1700 mcg DFE (1 mg Folic Acid) | 283%
Vitamin B12 (Cyanocobalamin) | 12 mcg | 429%
Calcium (Calcium Carbonate) | 200 mg | 15%
Iron (Ferrous Fumarate) | 27 mg | 100%
Zinc (Zinc Oxide) | 25 mg | 192%
Copper (Cupric Oxide) | 2 mg | 154%

Other Ingredients: Microcrystalline Cellulose, Croscarmellose Sodium, Stearic Acid, Magnesium Stearate, Silicon Dioxide, Coating (Beet Powder, Caramel, Carnauba Wax, Polyethylene Glycol, Polyvinyl Alcohol, Talc, Titanium Dioxide).

CONTAINS: SOY

DESCRIPTION

WesTab Plus is an orally administered prenatal/postnatal prescription dietary supplement for both lactating and non-lactating mothers and should be administered under the supervision of a licensed medical practitioner.

DIRECTIONS

Before, during and/or after pregnancy, one tablet daily with a meal, or as directed by a licensed medical practitioner.

WARNINGS

WARNING: Accidental overdose of iron-containing products is a leading cause of fatal poisoning in children under 6. KEEP THIS PRODUCT OUT OF REACH OF CHILDREN. In case of accidental overdose, call a doctor or poison control center immediately.

CAUTION

High levels of folic acid may, especially in older adults, hide signs of Vitamin B-12 deficiency (such as pernicious anemia), a condition that can cause nerve damage.

HEALTH CLAIM

Store at Controlled Room Temperature 15° – 30°C (59° – 86°F). Protect from light and moisture. Dispense in a tight, light-resistant container with child-resistant closure.

Call your licensed medical practitioner about side effects. To report a serious adverse event or obtain product information, contact Westminster Pharmaceuticals, LLC at 1-844-221-7294.

WesTab Plus are beige colored tablets, debossed with "267" on one side, dispensed in bottles of 100 tablets.

HEALTH CLAIM

Manufactured for:
Westminster Pharmaceuticals, LLC
Nashville, TN 37217

Rev. 07/23

PRINCIPAL DISPLAY PANEL - 100 Tablet Bottle Label

69367-267-01

Rx

WesTab Plus
PRENATAL/POSTNATAL

Prescription Dietary Supplement

TAMPER EVIDENT: DO NOT USE IF
SAFETY SEAL UNDER CAP IS
BROKEN OR MISSING.

100 Tablets

Westminster
Pharmaceuticals